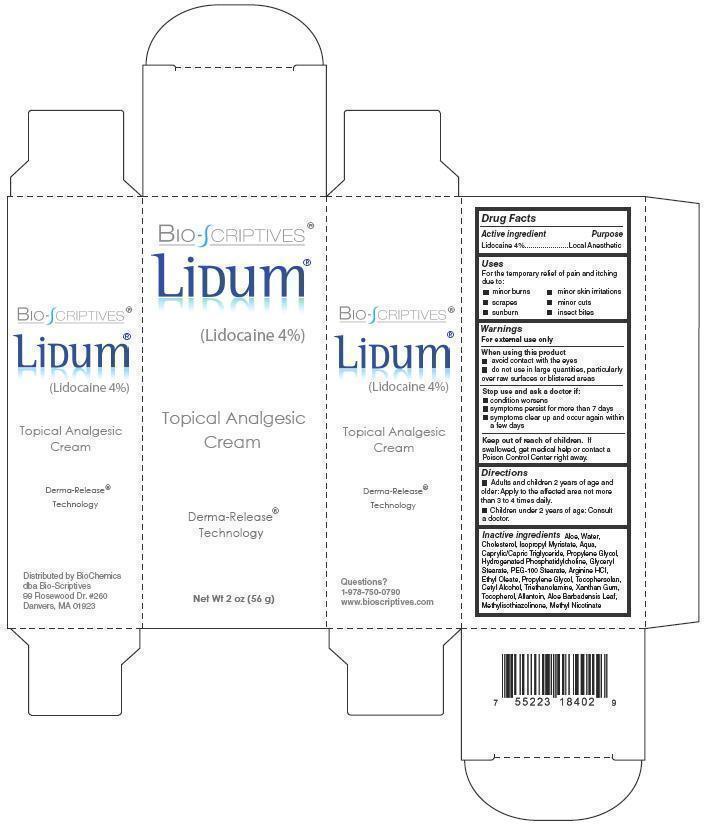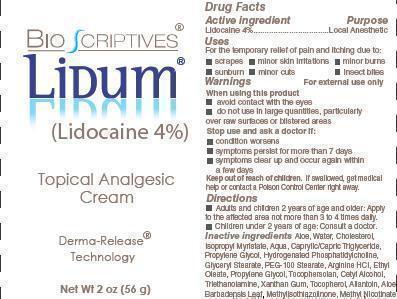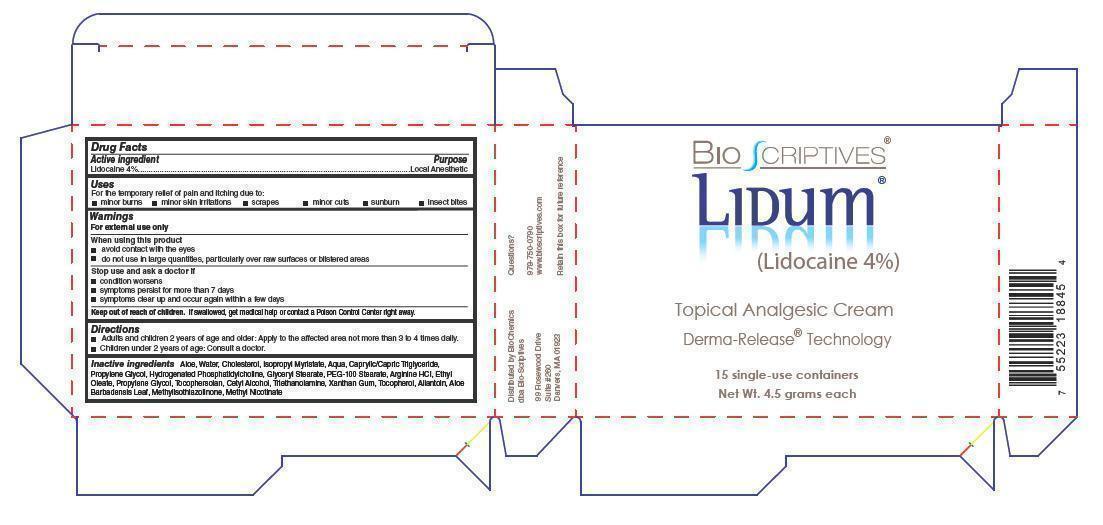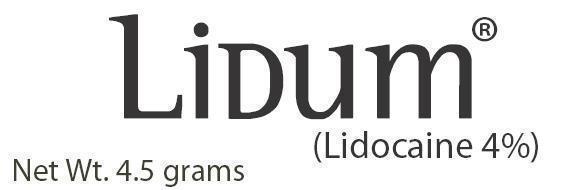 DRUG LABEL: Bio-Scriptives Lidum Topical Analgesic
NDC: 60608-017 | Form: CREAM
Manufacturer: Bio-Scriptives, Inc.
Category: prescription | Type: HUMAN PRESCRIPTION DRUG LABEL
Date: 20120309

ACTIVE INGREDIENTS: LIDOCAINE 2.8 g/56 g
INACTIVE INGREDIENTS: ALOE VERA LEAF; WATER; CHOLESTEROL; ISOPROPYL MYRISTATE; MEDIUM-CHAIN TRIGLYCERIDES; HYDROGENATED SOYBEAN LECITHIN; GLYCERYL MONOSTEARATE; POLYETHYLENE GLYCOL; ARGININE HYDROCHLORIDE; ETHYL OLEATE; PROPYLENE GLYCOL; TOCOPHERSOLAN; CETYL ALCOHOL; TROLAMINE; xanthan gum; ALPHA-TOCOPHEROL; ALLANTOIN; METHYLISOTHIAZOLINONE; METHYL NICOTINATE

Bio-Scriptives Lidum (Lidocaine 4%) Topical Analgesic

Drug Facts

Active Ingredients

Lidocaine 4%

Purpose

Local Analgesic

Uses

For the temporary relief of pain and itching due to:

■ minor burns

■ minor skin irritations

■ scrapes

■ minor cuts

■ sunburn

■ insect bites

Warnings

For external use only

When using this product

■ avoid contact with the eyes

■ do not use in large quantities, particularly over raw surfaces or blistered areas

Stop use and ask doctor if:

■ condition worsens

■ symptoms persist for more than 7 days

■ symptoms clear up and occur again within a few days

Keep out of reach of children

If swallowed, get medical help or contact a Poison Control Center right away.

Directions

■ Adults and children 2 years of age and older: Apply to the affected area not more than 3 to 4 times daily.

■ Children under 2 years of age: Consult a doctor.

Inactive Ingredients

Aloe, Water, Cholesterol, Isopropyl Myristate, Aqua Caprylic/Capric Triglyceride, Propylene Glycol, Hydrogenated Phosphatidylcholine, Glyceryl Stearate, PEG-100 Stearate, Arginine HCL, Ethyl Oleate, Propylene Glycol, Tocophersolan, Cetyl Alcohol, Triethanolamine, Xanthan Gum, Tocopherol, Allantoin, Aloe Barbadensis Leaf, Methylisothiazolinone, Methyl Nicotinate.